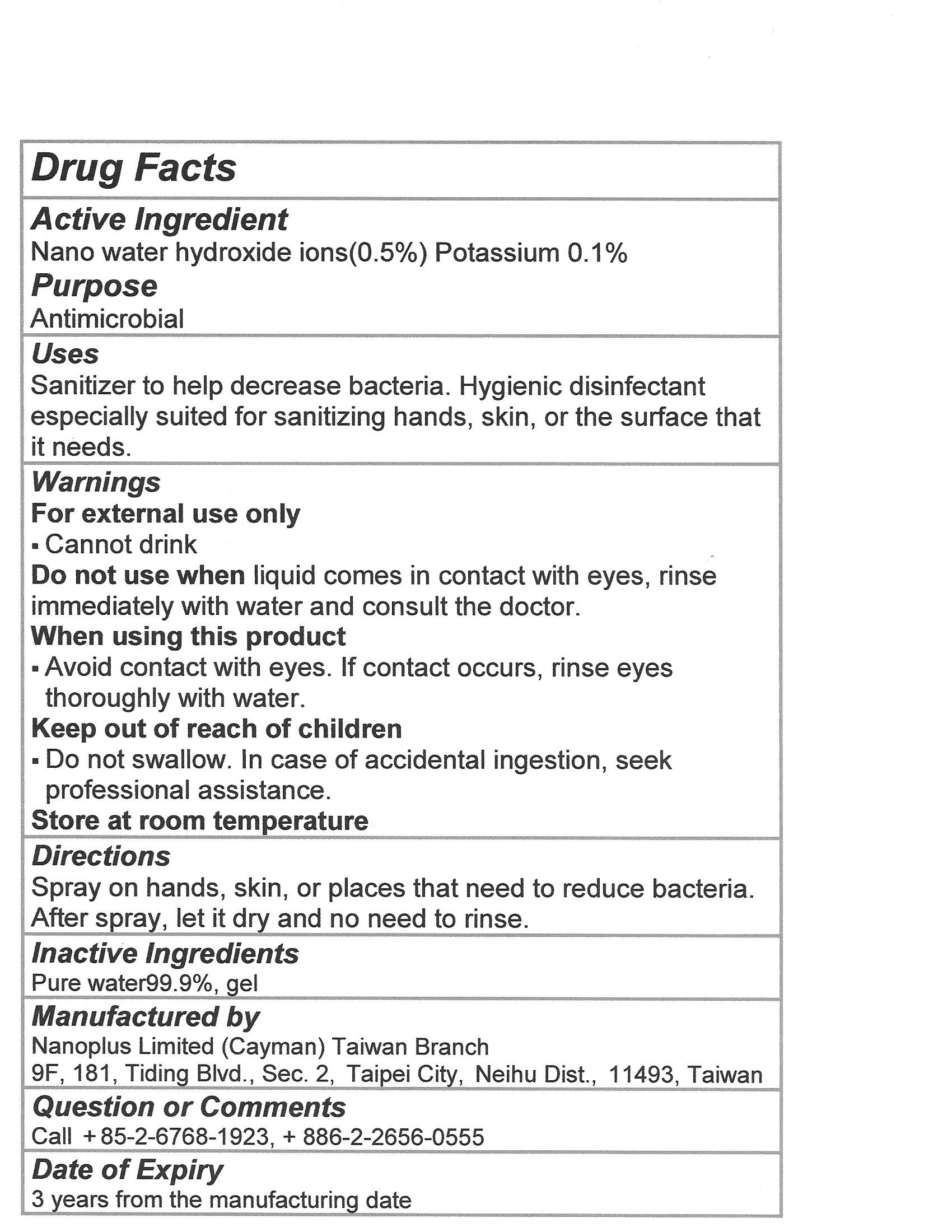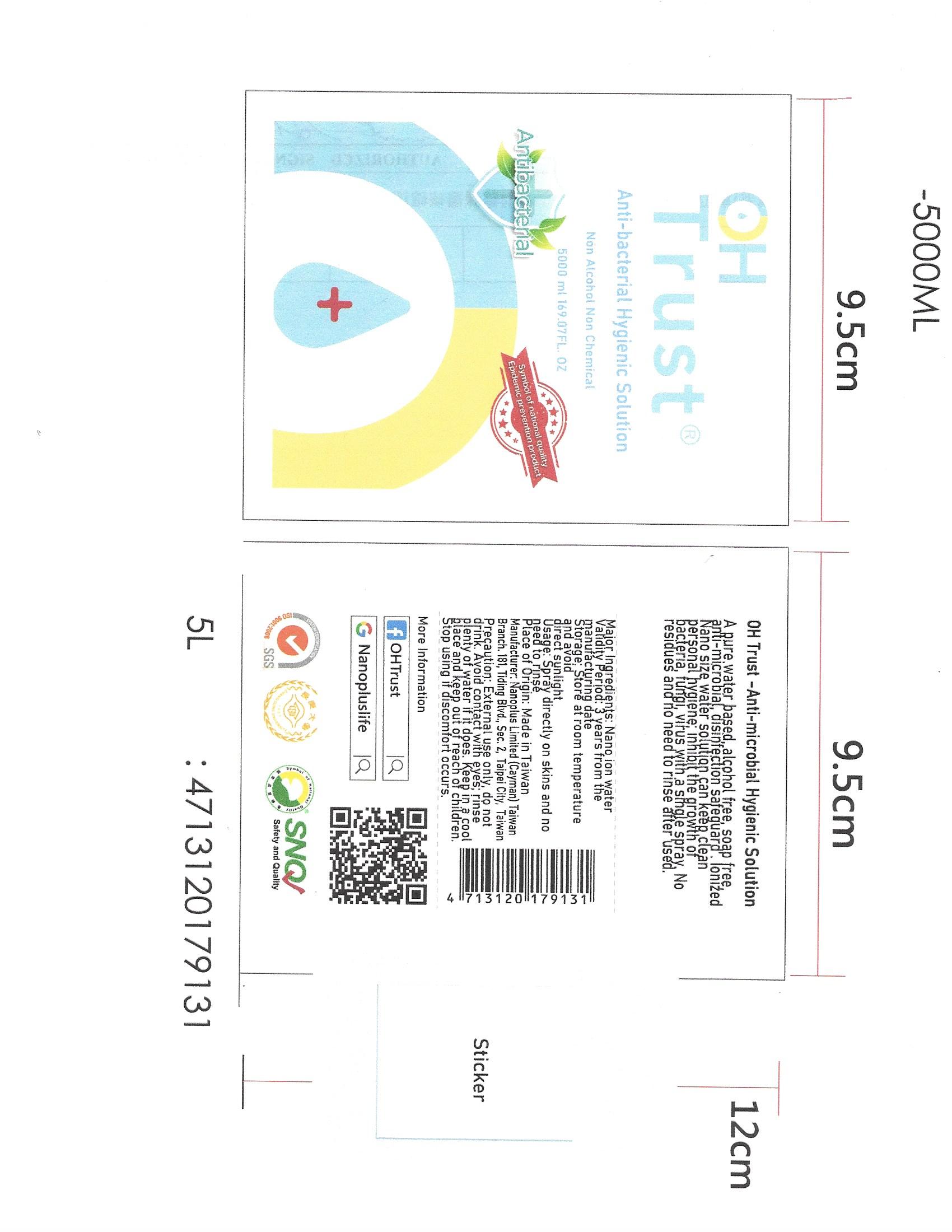 DRUG LABEL: OHTrust Nano Ion Water
NDC: 70970-002 | Form: LIQUID
Manufacturer: Nanoplus Limited (Cayman) Taiwan Branch
Category: otc | Type: HUMAN OTC DRUG LABEL
Date: 20220113

ACTIVE INGREDIENTS: POTASSIUM HYDROXIDE 0.2 g/100 mL
INACTIVE INGREDIENTS: WATER; GELATIN, UNSPECIFIED

Nanoplus 70970-002-50

Active Ingredient(s)

Nano Water hydroxide ions (0.5%) Potassium 0.1% Purpose: Antimicrobial

Purpose

Antimicrobial

Use

Sanitizer to help decrease bacteria. Hygienic disinfectant especially suited for sanitizing hands, skin or the surface that it needs.

Warnings

For external use only. Cannot drink

Do not use when liquid comes in contact with eyes, rinse immediately with water and consult the doctor

When using this product avoid contact with eyes. If contact occurs, rinse eyes thoroughly with water

Keep out of reach of children

Do not swallow. In case of accidental ingestion, seek professional assistance.

Store at room temperature

When using this product avoid contact with eyes. If contact occurs, rinse eyes thoroughly with water

Do not use when liquid comes in contact with eyes, rinse immediately with water and consult the doctor

Keep out of reach of children. Do not swallow. In case of accidental ingestion, seek professional assistance.

Keep out of reach of children. Do not swallow. In case of accidental ingestion, seek professional assistance.

Directions

Spray on hands, skin, or places that need to reduce bacteria. After spray, let it dry and no need to rinse.

Other information

Store at room temperature

Inactive ingredients

Pure Water 99.9%, gel

Package Label - Principal Display Panel

5000 mL NDC: 70970-002-50